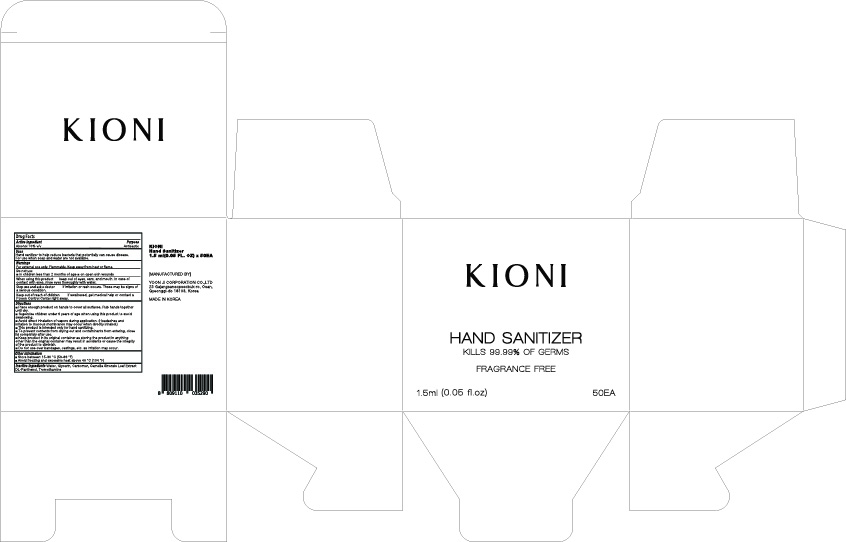 DRUG LABEL: KIONI HAND SANITIZER
NDC: 75024-700 | Form: GEL
Manufacturer: YOON JI CORPORATION CO.,LTD
Category: otc | Type: HUMAN OTC DRUG LABEL
Date: 20200921

ACTIVE INGREDIENTS: ALCOHOL 1.05 mL/1.5 mL
INACTIVE INGREDIENTS: GREEN TEA LEAF; GLYCERIN; CARBOMER HOMOPOLYMER, UNSPECIFIED TYPE; WATER; PANTHENOL; TROMETHAMINE

KIONI HAND SANITIZER 1.5 ml x 50 : 75024-700-50